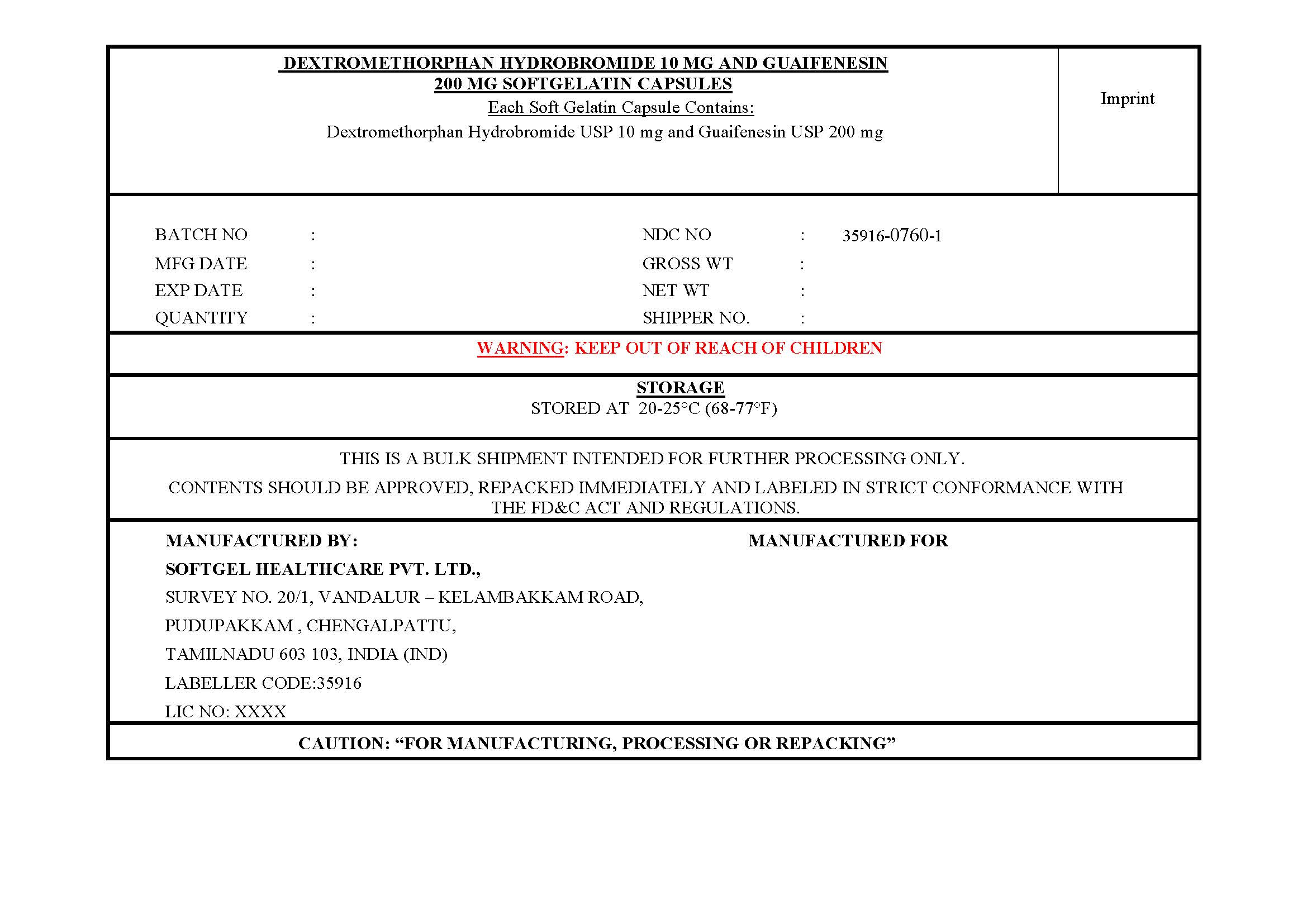 DRUG LABEL: Dextromethorphan Hbr,Guaifenesin
NDC: 35916-0760 | Form: CAPSULE, LIQUID FILLED
Manufacturer: SOFTGEL HEALTHCARE PRIVATE LIMITED
Category: otc | Type: HUMAN OTC DRUG LABEL
Date: 20260127

ACTIVE INGREDIENTS: GUAIFENESIN 200 mg/1 1; DEXTROMETHORPHAN HYDROBROMIDE 10 mg/1 1
INACTIVE INGREDIENTS: GLYCERIN; FD&C BLUE NO. 1; SORBITOL; WATER; POLYETHYLENE GLYCOL 400; D&C YELLOW NO. 10; TITANIUM DIOXIDE; GELATIN; POVIDONE K30

Dextromethorphan Hydrobromide 10 mg and Guaifenesin 200 mg Softgelatin Capsules

Active ingredient (in each soft gelatin capsule)

Dextromethorphan HBr USP 10mg

Guaifenesin USP 200mg

Purposes

Cough suppresent

Expectorant

Uses

- helps loosen phlegm (mucus) and thin bronchial secretions to rid the bronchial passageways of bothersome mucus and make coughs more productive
- temporarily relieves:
- cough due to minor throat and bronchial irritation as may occur with the common cold or inhaled irritants
- the intensity of coughing
- the impulse to cough to help you get to sleep

Warnings

Do not use

- if you are now taking a prescription monoamine oxidase inhibitor (MAOI) (certain drugs for depression, psychiatric, or emotional conditions, or Parkinson's disease), or for 2 weeks after stopping the MAOI drug. If you do not know if your prescription drug contains an MAOI, ask a doctor or pharmacist before taking this product.

Ask a doctor before use if you have

- persistent or chronic cough such as occurs with smoking,asthma,chronic bronchitis, or emphysema
- cough that occurs with too much phlegm(mucus)

When using this product do not use more than directed

Stop use and ask a doctor if

- cough lasts more than 7 days,comes back,or occur with fever, rash, or headache that lasts.

These could be signs of a serious condition.

PREGNANCY OR BREAST FEEDING

If pregnant or breast-feeding, ask a health professional before use.

Keep out of reach of children.

In case of overdose, get medical help or contact a poison control center right away.

Directions

- do not take more than 12 liquid gels in any 24-hour period
- adults and children 12 years of age and over: take 2 liquid gels every 4 hours
- children under 12 years of age: do not use

Other information

- store at 20-25°C (68-77°F)
- avoid excessive heat

Inactive ingredients

D&C yellow 10, FD&C blue 1, gelatin, glycerin, polyethylene glycol 400, povidone k-30, purified water, sorbitol sorbitan solution, titanium dioxide